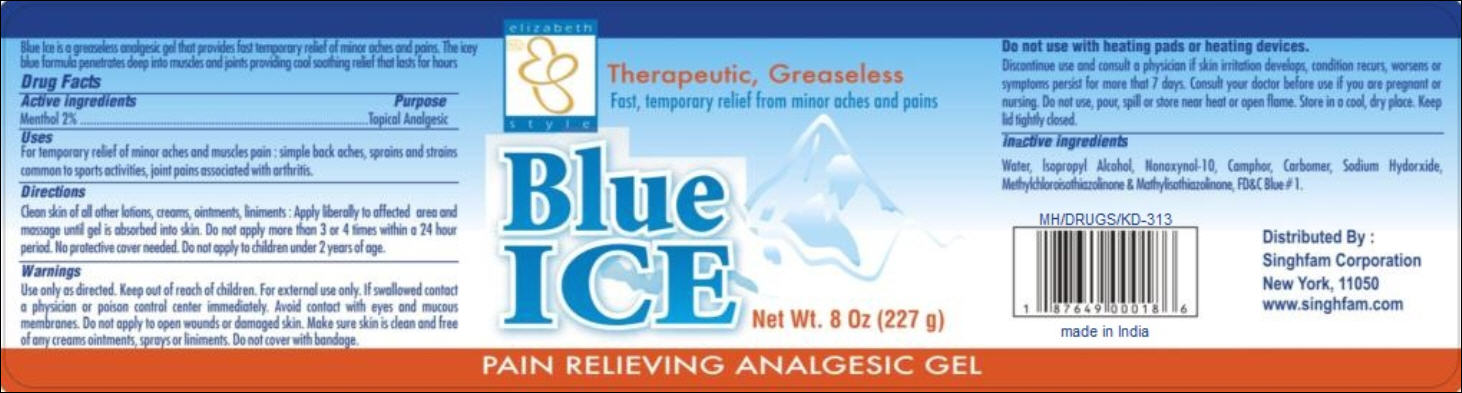 DRUG LABEL: Pain Relieving Analgesic
NDC: 52920-123 | Form: GEL
Manufacturer: Singhfam Corporation
Category: otc | Type: HUMAN OTC DRUG LABEL
Date: 20120120

ACTIVE INGREDIENTS: MENTHOL 4.54 g/1 g
INACTIVE INGREDIENTS: WATER; ISOPROPYL ALCOHOL; CAMPHOR (SYNTHETIC); CARBOMER 934; SODIUM HYDROXIDE; METHYLISOTHIAZOLINONE; FD&C BLUE NO. 1; NONOXYNOL-10

Analgesic Gel

Active Ingredients

Menthol 2%

Purpose

Topical Analgesic

Uses

For temporary relief of minor aches and muscles pain: simple back aches, sprains and strains common to sports activities, joint pains associated with arthritis.

Directions

Clean skin of all other lotions, creams, ointments, liniments: Apply liberally to affected area and massage until gel is absorbed into skin. Do not apply more than 3 or 4 times within a 24 hour period. No protective cover needed. Do not apply to children under 2 years of age.

Warnings

Use only as directed.

For external use only. If swallowed contact a physician or poison control center immediately. Avoid contact with eyes and mucous membranes. Do not apply to open wounds or damaged skin. Make sure skin is clean and free of any creams ointments, sprays or liniments. Do not cover with bandage.

Do not use

with heating pads or heating devices.

Discontinue use and consult a physician if skin irritation develops, condition recurs, worsens or symptoms persist for more that 7 days. Consult your doctor before use if you are pregnant or nursing. Do not use, pour, spill or store near heat or open flame. Store in a cool, dry place. Keep lid tightly closed.

Inactive Ingredients

Water, Isopropyl Alcohol, Nonoxynol-10, Camphor, Carbomer, Sodium Hydroxide, Methylchloroisothiazolinone & Mathylisothiazolinone, FD&C Blue #1.

PACKAGE LABEL

PRINCIPAL DISPLAY PANEL
elizabeth style
Therapeutic, Greaseless
Fast, temporary relief from minor aches and pains
Blue Ice
Net Wt. 8 Oz (227 g)
PAIN RELIEVING ANALGESIC GEL